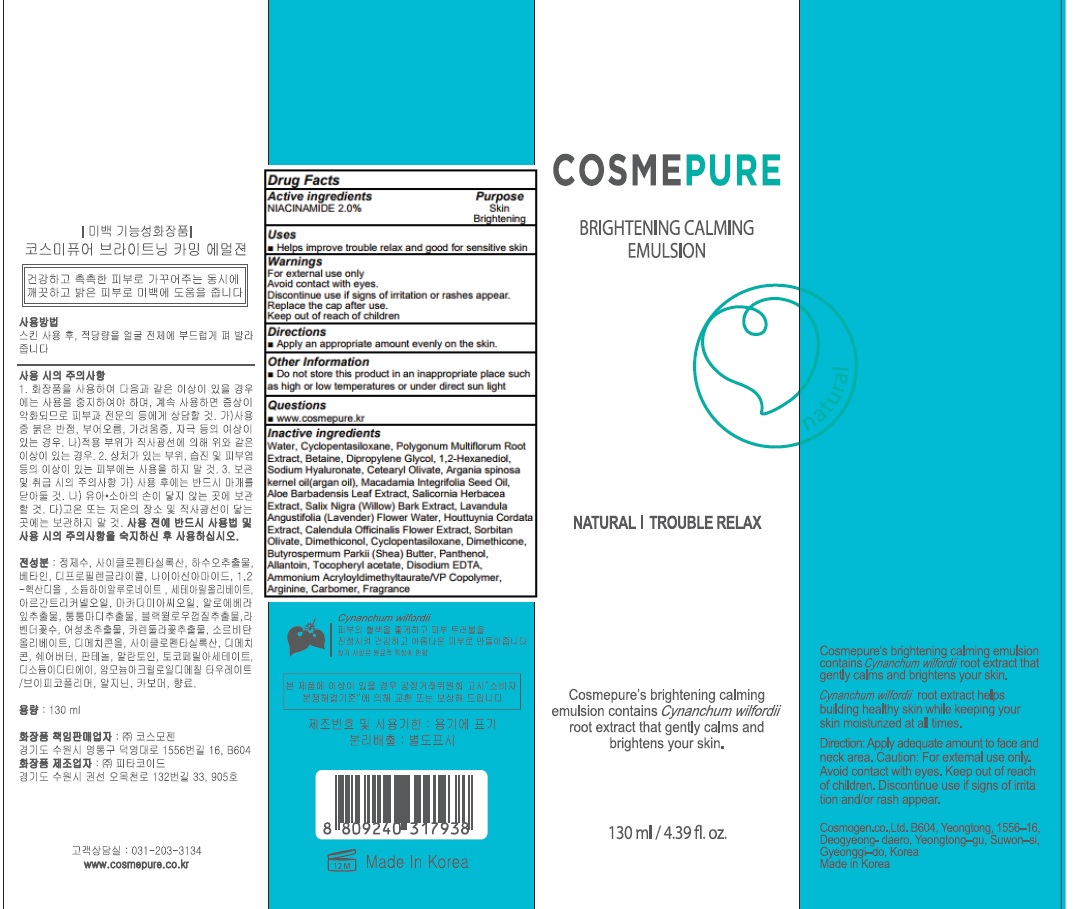 DRUG LABEL: COSMEPURE BRIGHTENING CALMING
NDC: 81418-070 | Form: EMULSION
Manufacturer: Cosmogen Co., Ltd.
Category: otc | Type: HUMAN OTC DRUG LABEL
Date: 20210304

ACTIVE INGREDIENTS: Niacinamide 2.6 g/130 mL
INACTIVE INGREDIENTS: Water; CYCLOMETHICONE 5; REYNOUTRIA MULTIFLORA ROOT

ACTIVE INGREDIENT

Niacinamide 2.0%

INACTIVE INGREDIENTS

Water, Cyclopentasiloxane, Polygonum Multiflorum Root Extract, Betaine, Dipropylene Glycol, 1,2-Hexanediol, Sodium Hyaluronate, Cetearyl Olivate, Argania spinosa kernel oil(argan oil), Macadamia Integrifolia Seed Oil, Aloe Barbadensis Leaf Extract, Salicornia Herbacea Extract, Salix Nigra (Willow) Bark Extract, Lavandula Angustifolia (Lavender) Flower Water, Houttuynia Cordata Extract, Calendula Officinalis Flower Extract, Sorbitan Olivate, Dimethiconol, Cyclopentasiloxane, Dimethicone, Butyrospermum Parkii (Shea) Butter, Panthenol, Allantoin, Tocopheryl acetate, Disodium EDTA, Ammonium Acryloyldimethyltaurate/VP Copolymer, Arginine, Carbomer, Fragrance

PURPOSE

Skin brightening

WARNINGS

For external use only
Avoid contact with eyes.
Discontinue use if signs of irritation or rashes appear.
Replace the cap after use.
Keep out of reach of children

KEEP OUT OF REACH OF CHILDREN

Uses

■ Helps improve trouble relax and good for sensitive skin

Directions

■ Apply an appropriate amount evenly on the skin.

Other information

■ Do not store this product in an inappropriate place such as high or low temperatures or under direct sun light

QUESTIONS

■ www.cosmepure.kr